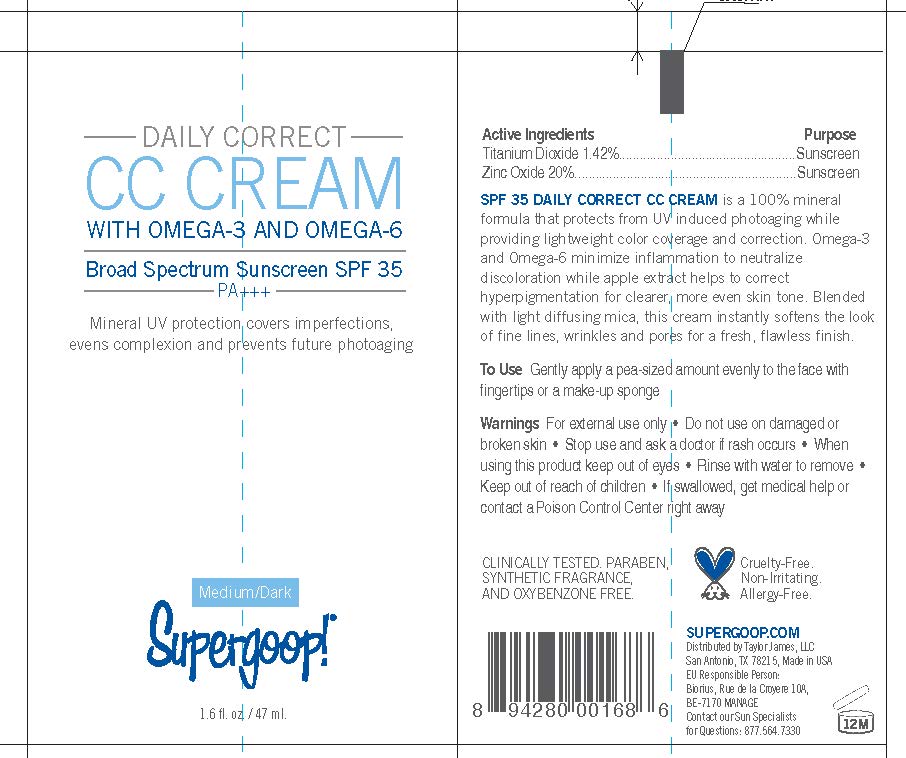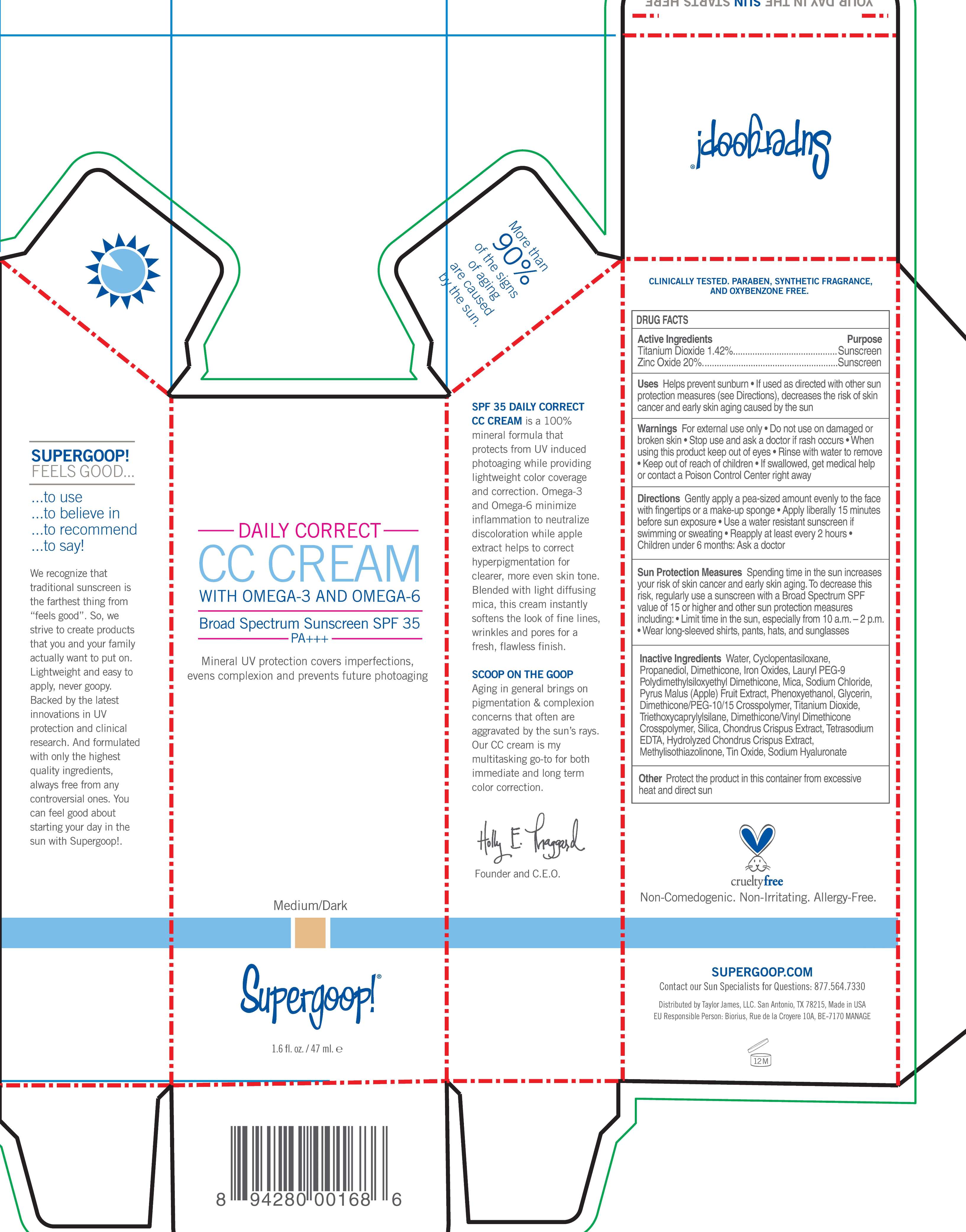 DRUG LABEL: CC Daily Correct Broad Spectrum SPF 35 Sunscreen Medium to Dark

NDC: 75936-122 | Form: CREAM
Manufacturer: TAYLOR JAMES, LTD.
Category: otc | Type: HUMAN OTC DRUG LABEL
Date: 20201112

ACTIVE INGREDIENTS: TITANIUM DIOXIDE 1.42 g/100 mL; ZINC OXIDE 20 g/100 mL
INACTIVE INGREDIENTS: WATER; CYCLOMETHICONE 5; PROPANEDIOL; DIMETHICONE; FERRIC OXIDE RED; FERRIC OXIDE YELLOW; FERROSOFERRIC OXIDE; MICA; SODIUM CHLORIDE; APPLE; PHENOXYETHANOL; GLYCERIN; TRIETHOXYCAPRYLYLSILANE; SILICON DIOXIDE; CHONDRUS CRISPUS; METHYLISOTHIAZOLINONE; STANNIC OXIDE; HYALURONATE SODIUM

CC Daily Correct SPF 35 Sunscreen Medium to Dark

Active Ingredients purpose

Titanium Dioxide 1.42 % Sunscreen

Zinc Oxide 20% Sunscreen

Uses

Helps prevent sunburn

If used as directed with other sun protection measures (see Directions), decreases the risk of skin cancer and early skin aging caused by the sun.

Keep out of reach of children

Stop use and ask a doctor if rash occurs

Warnings For external use only

Do not use on damaged or broken skin

When using this product keep out of eyes

Rinse with water to remove

If swallowed, get medical help or contact a Poison Control Center right away

DOSAGE AND ADMINISTRATION

Directions Apply liberally 15 minutes before sun exposure

Use a water resistant sunscreen if swimming or sweating

Reapply at least every 2 hours

Children under 6 months: Ask a doctor

Sun Protection Measures Spending time in the sun increases your skin of skin cancer and early skin aging. To decrease this risk, regularly use a sunscreen with a Broad Spectrum SPF value of 15 or higher and other sun protection measures including:

Limit time in the sun especially from 10 a.m.- 2 p.m.

Wear long-sleeved shirts, pants, pants hats and sunglasses

INACTIVE INGREDIENT

Inactive Ingredients Water, Cyclopentasiloxane, Propanediol, Dimethicone, Iron Oxides, Lauryl PEG-9 Polydimethylsiloxyethyl Dimethicone, Mica, Sodium Chloride, Pyrus Malus (apple) Fruit Extract, Phenoxyethanol, Glycerin, Dimethicone/PEG-10/15 Crosspolymer, Titanium Dioxide, Triethoxycaprylylsilane, Dimethicone/Vinyl Dimethicone Crosspolymer, Silica, Chondrus Crispus Extract, Tetrasodium EDTA, Hydrolyzed Chondrus Crispus Extract, Methylisothiazolinone, Tin Oxide, Sodium Hyaluronate.

PACKAGE LABEL

CC cream Daily Correct Broad Spectrum SPF 35 Sunscreen

Medium to Dark

Self-Adjusting Shade

PA +++

Supergoop

Paraben, Fragrance, and Oxybenzone Free

1.6 fl. oz. / 47